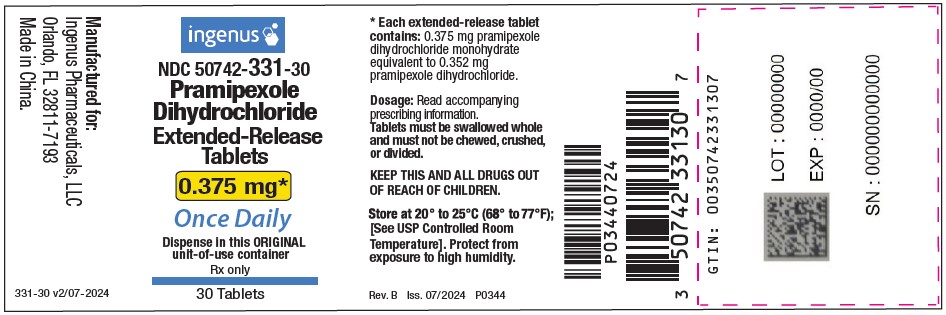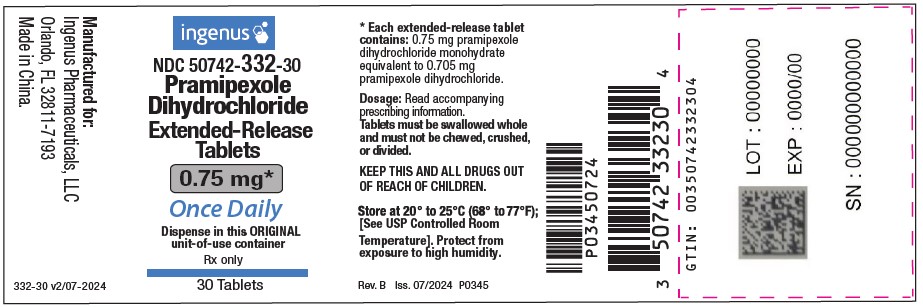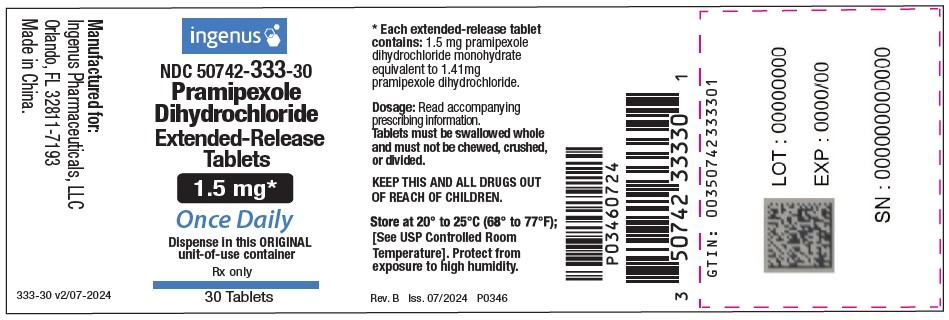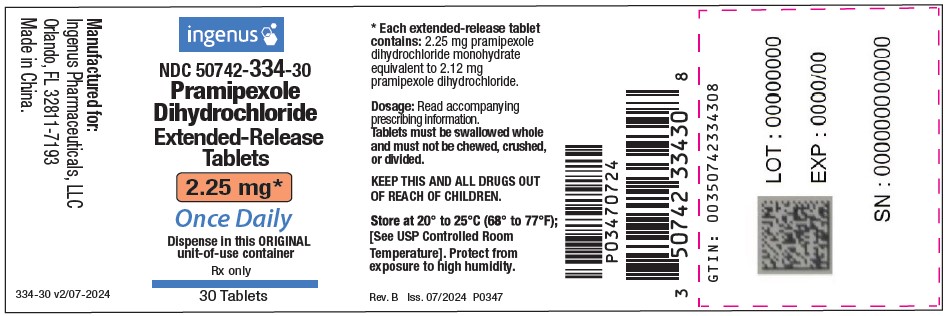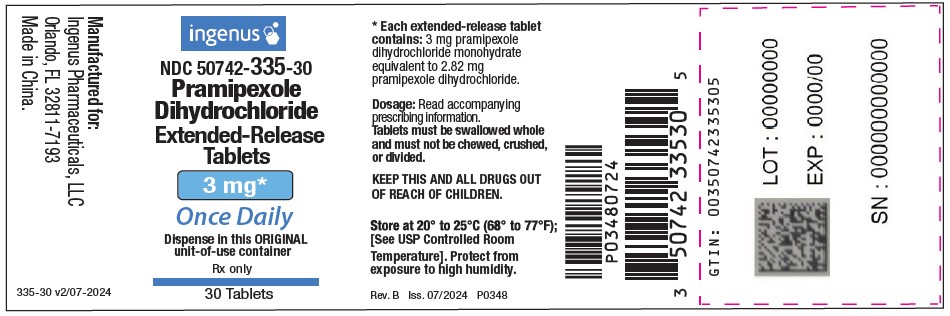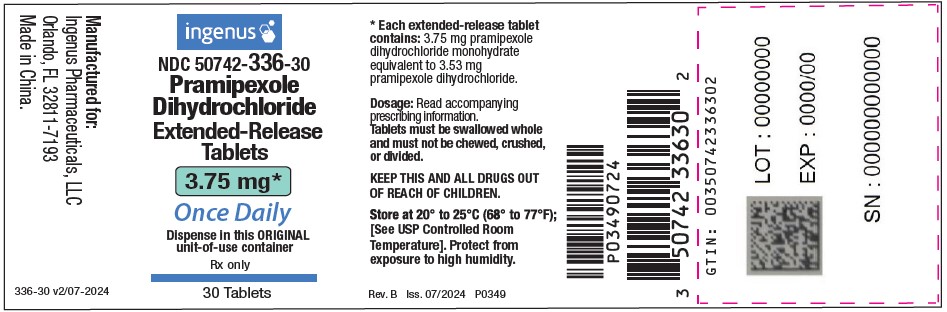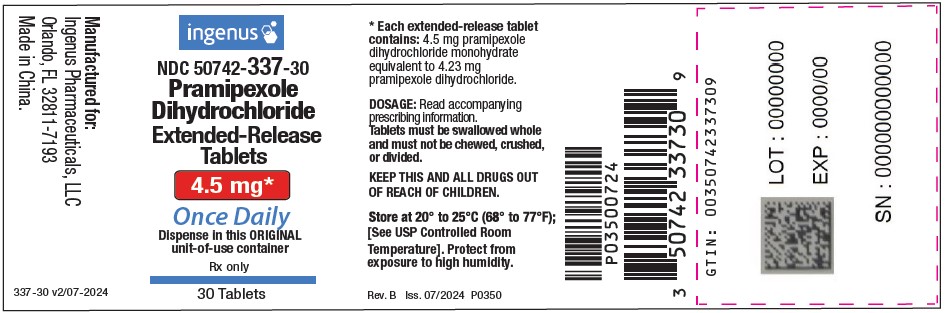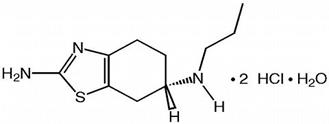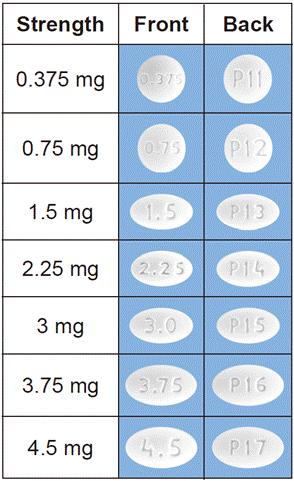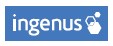 DRUG LABEL: Pramipexole dihydrochloride
NDC: 50742-331 | Form: TABLET, EXTENDED RELEASE
Manufacturer: Ingenus Pharmaceuticals, LLC
Category: prescription | Type: HUMAN PRESCRIPTION DRUG LABEL
Date: 20250424

ACTIVE INGREDIENTS: PRAMIPEXOLE DIHYDROCHLORIDE 0.375 mg/1 1
INACTIVE INGREDIENTS: HYPROMELLOSE 2208 (15000 MPA.S); STARCH, CORN; MICROCRYSTALLINE CELLULOSE; SODIUM LAURYL SULFATE; SODIUM METABISULFITE; MAGNESIUM STEARATE

HIGHLIGHTS OF PRESCRIBING INFORMATION

These highlights do not include all the information needed to use PRAMIPEXOLE DIHYDROCHLORIDE EXTENDED-RELEASE TABLETS safely and effectively. See full prescribing information for PRAMIPEXOLE DIHYDROCHLORIDE EXTENDED-RELEASE TABLETS.
PRAMIPEXOLE DIHYDROCHLORIDE extended-release tablets, for oral use
Initial U.S. Approval: 1997

1 INDICATIONS AND USAGE

Pramipexole dihydrochloride extended- release tablet is a non-ergot dopamine agonist indicated for the treatment of Parkinson's disease (PD) (1)

2 DOSAGE AND ADMINISTRATION

- Pramipexole dihydrochloride extended- release tablets are taken once daily, with or without food (2.1)
- Tablets must be swallowed whole and must not be chewed, crushed, or divided (2.1)
- Starting dose is 0.375 mg given once daily (2.2)
- Dose may be increased gradually, not more frequently than every 5 to 7 days, first to 0.75 mg per day and then by 0.75 mg increments up to a maximum recommended dose of 4.5 mg per day. Assess therapeutic response and tolerability at a minimal interval of 5 days or longer after each dose increment (2.2)
- Patients may be switched overnight from immediate-release pramipexole tablets to pramipexole dihydrochloride extended- release tablets at the same daily dose. Dose adjustment may be needed in some patients (2.3)
- Pramipexole dihydrochloride extended- release tablets should be discontinued gradually (2.2)

3 DOSAGE FORMS AND STRENGTHS

Extended-release tablets: 0.375 mg, 0.75 mg, 1.5 mg, 2.25 mg, 3 mg, 3.75 mg, and 4.5 mg (3)

4 CONTRAINDICATIONS

None.

5 WARNINGS AND PRECAUTIONS

- Falling Asleep During Activities of Daily Living: Sudden onset of sleep may occur without warning; advise patients to report symptoms (5.1)
- Symptomatic Orthostatic Hypotension: Monitor closely especially during dose escalation (5.2)
- Impulse Control/Compulsive Behaviors: Patients may experience compulsive behaviors and other intense urges (5.3)
- Hallucinations and Psychotic-like Behavior: May occur; risk increases with age (5.4)
- Dyskinesia: May be caused or exacerbated by pramipexole dihydrochloride extended- release tablets (5.5)
- Postural Deformity: Consider reducing the dose or discontinuing pramipexole dihydrochloride extended-release tablets if postural deformity occurs (5.6)

6 ADVERSE REACTIONS

Most common adverse reactions (incidence ≥5% and greater than placebo):

- Early PD without levodopa: somnolence, nausea, constipation, dizziness, fatigue, hallucinations, dry mouth, muscle spasms, and peripheral edema (6.1)
- Advanced PD with levodopa: dyskinesia, nausea, constipation, hallucinations, headache, and anorexia (6.1)

To report SUSPECTED ADVERSE REACTIONS, contact Ingenus Pharmaceuticals, LLC Toll-Free at 1-877-748-1970 or FDA at 1-800-FDA-1088 or www.fda.gov/medwatch.

7 DRUG INTERACTIONS

Dopamine antagonists: May diminish the effectiveness of pramipexole (7.1)

8 USE IN SPECIFIC POPULATIONS

Pregnancy: Based on animal data, may cause fetal harm (8.1)

FULL PRESCRIBING INFORMATION

1 INDICATIONS AND USAGE

Pramipexole dihydrochloride extended- release tablets are indicated for the treatment of Parkinson's disease.

2 DOSAGE AND ADMINISTRATION

2.1 General Dosing Considerations

Pramipexole dihydrochloride extended- release tablets are taken orally once daily, with or without food.

Pramipexole dihydrochloride extended- release tablets must be swallowed whole and must not be chewed, crushed, or divided.

If a significant interruption in therapy with pramipexole dihydrochloride extended- release tablets has occurred, re-titration of therapy may be warranted.

2.2 Recommended Dosage

The starting dose is 0.375 mg given once per day. Based on efficacy and tolerability, dosages may be increased gradually, not more frequently than every 5 to 7 days, first to 0.75 mg per day and then by 0.75 mg increments up to a maximum recommended dose of 4.5 mg per day.

In clinical trials, dosage was initiated at 0.375 mg/day and gradually titrated based on individual therapeutic response and tolerability. Doses greater than 4.5 mg/day have not been studied in clinical trials. Patients should be assessed for therapeutic response and tolerability at a minimal interval of 5 days or longer after each dose increment [see Clinical Studies (14)].

Due to the flexible dose design used in clinical trials, specific dose-response information could not be determined [see Clinical Studies (14)].

Pramipexole dihydrochloride extended- release tablets may be tapered off at a rate of 0.75 mg per day until the daily dose has been reduced to 0.75 mg. Thereafter, the dose may be reduced by 0.375 mg per day [see Warnings and Precautions (5.10, 5.11)].

Recommended Dosage in Patients with Renal Impairment

In patients with moderate renal impairment (creatinine clearance between 30 and 50 mL/min), pramipexole dihydrochloride extended- release tablets should initially be taken every other day. Caution should be exercised and careful assessment of therapeutic response and tolerability should be made before increasing to daily dosing after one week, and before any additional titration in 0.375 mg increments up to 2.25 mg per day. Dose adjustment should occur no more frequently than at weekly intervals.

Pramipexole dihydrochloride extended- release tablets have not been studied in patients with severe renal impairment (creatinine clearance <30 mL/min) or patients on hemodialysis, and are not recommended in these patients.

2.3 Switching from Immediate-Release Pramipexole Tablets to Pramipexole Dihydrochloride Extended- Release Tablets

Patients with Parkinson's disease may be switched overnight from immediate-release pramipexole tablets to pramipexole dihydrochloride extended-release tablets at the same daily dose. When switching between immediate-release pramipexole tablets and pramipexole dihydrochloride extended-release tablets, patients should be monitored to determine if dosage adjustment is necessary.

3 DOSAGE FORMS AND STRENGTHS

- 0.375 mg white or off-white, round, biconvex tablets debossed "0.375" on one side and "P11" on the other side. Each extended-release tablet contains 0.375 mg pramipexole dihydrochloride monohydrate equivalent to 0.352 mg pramipexole dihydrochloride.
- 0.75 mg white or off-white, round, biconvex tablets debossed "0.75" on one side and "P12" on the other side. Each extended-release tablet contains 0.75 mg pramipexole dihydrochloride monohydrate equivalent to 0.705 mg pramipexole dihydrochloride.
- 1.5 mg white or off-white, oval, biconvex tablets debossed "1.5" on one side and "P13" on the other side. Each extended-release tablet contains 1.5 mg pramipexole dihydrochloride monohydrate equivalent to 1.41 mg pramipexole dihydrochloride.
- 2.25 mg white or off-white, oval, biconvex tablets debossed "2.25" on one side and "P14" on the other side. Each extended-release tablet contains 2.25 mg pramipexole dihydrochloride monohydrate equivalent to 2.12 mg pramipexole dihydrochloride.
- 3 mg white or off-white, oval, biconvex tablets debossed "3.0" on one side and "P15" on the other side. Each extended-release tablet contains 3 mg pramipexole dihydrochloride monohydrate equivalent to 2.82 mg pramipexole dihydrochloride.
- 3.75 mg white or off-white, oval, biconvex tablets debossed "3.75" on one side and "P16" on the other side. Each extended-release tablet contains 3.75 mg pramipexole dihydrochloride monohydrate equivalent to 3.53 mg pramipexole dihydrochloride.
- 4.5 mg white or off-white, oval, biconvex tablets debossed "4.5" on one side and "P17" on the other side. Each extended-release tablet contains 4.5 mg pramipexole dihydrochloride monohydrate equivalent to 4.23 mg pramipexole dihydrochloride.

4 CONTRAINDICATIONS

None.

5 WARNINGS AND PRECAUTIONS

5.1 Falling Asleep During Activities of Daily Living and Somnolence

Patients treated with pramipexole have reported falling asleep while engaged in activities of daily living, including the operation of motor vehicles, which sometimes resulted in accidents. Although many of these patients reported somnolence while on pramipexole tablets, some perceived that they had no warning signs (sleep attack) such as excessive drowsiness, and believed that they were alert immediately prior to the event. Some of these events had been reported as late as one year after the initiation of treatment. In placebo- controlled clinical trials in Parkinson's disease, the sudden onset of sleep or sleep attacks were reported in 8 of 387 (2%) patients treated with pramipexole dihydrochloride extended-release tablets compared to 2 of 281 (1%) patients on placebo.

In early Parkinson's disease, somnolence was reported in 36% of 223 patients treated with pramipexole dihydrochloride extended-release tablets, median dose 3.0 mg/day, compared to 15% of 103 patients on placebo. In advanced Parkinson's disease, somnolence was reported in 15% of 164 patients treated with pramipexole dihydrochloride extended-release tablets, median dose 3 mg/day, compared to 16% of 178 patients on placebo. It has been reported that falling asleep while engaged in activities of daily living usually occurs in a setting of preexisting somnolence, although patients may not give such a history. For this reason, prescribers should reassess patients for drowsiness or sleepiness, especially since some of the events occur well after the start of treatment. Prescribers should also be aware that patients may not acknowledge drowsiness or sleepiness until directly questioned about drowsiness or sleepiness during specific activities.

Before initiating treatment with pramipexole dihydrochloride extended-release tablets, advise patients of the potential to develop drowsiness, and specifically ask about factors that may increase the risk for somnolence such as the use of concomitant sedating medications or alcohol, the presence of sleep disorders, and concomitant medications that increase pramipexole plasma levels (e.g., cimetidine) [see Clinical Pharmacology (12.3)]. If a patient develops significant daytime sleepiness or episodes of falling asleep during activities that require active participation (e.g., conversations, eating, etc.), pramipexole dihydrochloride extended-release tablets should ordinarily be discontinued. If a decision is made to continue pramipexole dihydrochloride extended-release tablets, advise patients not to drive and to avoid other potentially dangerous activities that might result in harm if the patients become somnolent. While dose reduction reduces the degree of somnolence, there is insufficient information to establish that dose reduction will eliminate episodes of falling asleep while engaged in activities of daily living.

5.2 Symptomatic Orthostatic Hypotension

Dopamine agonists, in clinical studies and clinical experience, appear to impair the systemic regulation of blood pressure, with resulting orthostatic hypotension, especially during dose escalation. Parkinson’s disease patients, in addition, appear to have an impaired capacity to respond to an orthostatic challenge. For these reasons, Parkinson’s disease patients being treated with dopaminergic agonists, including pramipexole dihydrochloride extended-release tablets, ordinarily require careful monitoring for signs and symptoms of orthostatic hypotension, especially during dose escalation, and should be informed of this risk. In placebo-controlled clinical trials in Parkinson’s disease, symptomatic orthostatic hypotension was reported in 10 of 387 (3%) patients treated with pramipexole dihydrochloride extended-release tablets compared to 3 of 281 (1%) patients on placebo. One patient of 387 on pramipexole dihydrochloride extended-release tablets discontinued treatment due to hypotension.

5.3 Impulse Control/Compulsive Behaviors

Case reports and the results of cross-sectional studies suggest that patients can experience intense urges to gamble, increased sexual urges, intense urges to spend money, binge eating, and/or other intense urges, and the inability to control these urges while taking one or more of the medications, including pramipexole dihydrochloride extended-release tablets, that increase central dopaminergic tone. In some cases, although not all, these urges were reported to have stopped when the dose was reduced or the medication was discontinued. Because patients may not recognize these behaviors as abnormal, it is important for prescribers to specifically ask patients or their caregivers about the development of new or increased gambling urges, sexual urges, uncontrolled spending or other urges while being treated with pramipexole dihydrochloride extended-release tablets for Parkinson’s disease. Physicians should consider dose reduction or stopping the medication if a patient develops such urges while taking pramipexole dihydrochloride extended-release tablets.
A total of 1056 patients with Parkinson’s disease who participated in two pramipexole dihydrochloride extended-release tablets placebo-controlled studies of up to 33 weeks duration were specifically asked at each visit about the occurrence of these symptoms. A total of 14 of 387 (4%) treated with pramipexole dihydrochloride extended-release tablets, 12 of 388 (3%) treated with immediate-release pramipexole tablets, and 4 of 281 (1%) treated with placebo reported compulsive behaviors, including pathological gambling, hypersexuality, and/or compulsive buying.

5.4 Hallucinations and Psychotic-like Behavior

In placebo-controlled clinical trials in Parkinson's disease, hallucinations (visual or auditory or mixed) were reported in 25 of 387 (6%) patients treated with pramipexole dihydrochloride extended-release tablets compared to 5 of 281 (2%) patients receiving placebo. Hallucinations led to discontinuation of treatment in 5 of 387 (1%) patients on pramipexole dihydrochloride extended-release tablets.

Age appears to increase the risk of hallucinations attributable to pramipexole. In placebo-controlled clinical trials in Parkinson's disease, hallucinations were reported in 15 of 162 (9%) patients ≥65 years of age taking pramipexole dihydrochloride extended-release tablets compared to 10 of 225 (4%) patients <65 years of age taking pramipexole dihydrochloride extended-release tablets.

Postmarketing reports with dopamine agonists, including pramipexole dihydrochloride extended-release tablets, indicate that patients with Parkinson's disease may experience new or worsening mental status and behavioral changes, which may be severe, including psychotic-like behavior during treatment with pramipexole dihydrochloride extended-release tablets or after starting or increasing the dose of pramipexole dihydrochloride extended-release tablets. Other drugs prescribed to improve the symptoms of Parkinson's disease can have similar effects on thinking and behavior. This abnormal thinking and behavior can consist of one or more of a variety of manifestations including paranoid ideation, delusions, hallucinations, confusion, psychotic-like behavior, symptoms of mania (e.g., insomnia, psychomotor agitation), disorientation, aggressive behavior, agitation, and delirium.

Patients with a major psychotic disorder should ordinarily not be treated with dopamine agonists, including pramipexole dihydrochloride extended-release tablets, because of the risk of exacerbating the psychosis. In addition, certain medications used to treat psychosis may exacerbate the symptoms of Parkinson's disease and may decrease the effectiveness of pramipexole dihydrochloride extended-release tablets [see Drug Interactions (7.1)].

5.5 Dyskinesia

Pramipexole dihydrochloride extended- release tablets may cause or exacerbate preexisting dyskinesia.

5.6 Postural Deformity

Postural deformities, including antecollis, camptocormia (Bent Spine Syndrome), and pleurothotonus (Pisa Syndrome), have been reported in patients after starting or increasing the dose of pramipexole dihydrochloride extended-release tablets. Postural deformity may occur several months after starting treatment or increasing the dose. Reducing the dose or discontinuing pramipexole dihydrochloride extended-release tablets has been reported to improve postural deformity in some patients, and should be considered if postural deformity occurs.

5.7 Renal Impairment

The elimination of pramipexole is dependent on renal function [see Clinical Pharmacology (12.3)]. Patients with mild renal impairment (a creatinine clearance above 50 mL/min) require no reduction in daily dose. Pramipexole dihydrochloride extended-release tablets have not been studied in patients with moderate to severe renal impairment (creatinine clearance <50 mL/min) or on hemodialysis [see Dosage and Administration (2.2), Use in Specific Populations (8.6), and Clinical Pharmacology (12.3)].

5.8 Rhabdomyolysis

In the clinical development program for immediate-release pramipexole tablets, a single case of rhabdomyolysis occurred in a 49-year-old male with advanced Parkinson's disease. The patient was hospitalized with an elevated CPK (10,631 IU/L). The symptoms resolved with discontinuation of the medication.

Advise patients to contact a physician if they experience any unexplained muscle pain, tenderness, or weakness, as these may be symptoms of rhabdomyolysis.

5.9 Retinal Pathology

Human Data

A two-year open-label, randomized, parallel-group safety study of retinal deterioration and vision compared immediate-release pramipexole tablets and immediate-release ropinirole. Two hundred thirty four Parkinson's disease patients (115 on pramipexole, mean dose 3.0 mg/day and 119 on ropinirole, mean dose 9.5 mg/day) were evaluated using a panel of clinical ophthalmological assessments. Of 234 patients who were evaluable, 196 had been treated for two years and 29 were judged to have developed clinical abnormalities that were considered meaningful (19 patients in each treatment arm had received treatment for less than two years).There was no statistical difference in retinal deterioration between the treatment arms; however, the study was only capable of detecting a very large difference between treatments. In addition, because the study did not include an untreated comparison group (placebo treated), it is unknown whether the findings reported in patients treated with either drug are greater than the background rate in an aging population.

Animal Data

Pathologic changes (degeneration and loss of photoreceptor cells) were observed in the retina of albino rats in a 2-year carcinogenicity study. While retinal degeneration was not diagnosed in pigmented rats treated for 2 years, a thinning in the outer nuclear layer of the retina was slightly greater in rats given drug compared with controls. Evaluation of the retinas of albino mice, monkeys, and minipigs did not reveal similar changes. The potential significance of this effect for humans has not been established, but cannot be disregarded because disruption of a mechanism that is universally present in vertebrates (i.e., disk shedding) may be involved [see Nonclinical Toxicology (13.2)].

5.10 Events Reported with Dopaminergic Therapy

Although the events enumerated below may not have been reported with the use of pramipexole in its development program, they are associated with the use of other dopaminergic drugs. The expected incidence of these events, however, is so low that even if pramipexole caused these events at rates similar to those attributable to other dopaminergic therapies, it would be unlikely that even a single case would have occurred in a cohort of the size exposed to pramipexole in studies to date.

Hyperpyrexia and Confusion

Although not reported with pramipexole in the clinical development program, a symptom complex resembling the neuroleptic malignant syndrome (characterized by elevated temperature, muscular rigidity, altered consciousness, and autonomic instability), with no other obvious etiology, has been reported in association with rapid dose reduction, withdrawal of, or changes in dopaminergic therapy. If possible, avoid sudden discontinuation or rapid dose reduction in patients taking pramipexole dihydrochloride extended-release tablets. If the decision is made to discontinue pramipexole dihydrochloride extended-release tablets, the dose should be tapered to reduce the risk of hyperpyrexia and confusion [see Dosage and Administration (2.2)].

Fibrotic Complications

Cases of retroperitoneal fibrosis, pulmonary infiltrates, pleural effusion, pleural thickening, pericarditis, and cardiac valvulopathy have been reported in patients treated with ergot-derived dopaminergic agents. While these complications may resolve when the drug is discontinued, complete resolution does not always occur.

Although these adverse events are believed to be related to the ergoline structure of these compounds, whether other, non-ergot derived dopamine agonists can cause them is unknown.

Cases of possible fibrotic complications, including peritoneal fibrosis, pleural fibrosis, and pulmonary fibrosis have been reported in the postmarketing experience with immediate-release pramipexole tablets. While the evidence is not sufficient to establish a causal relationship between pramipexole and these fibrotic complications, a contribution of pramipexole cannot be completely ruled out.

5.11 Withdrawal Symptoms

Symptoms including apathy, anxiety, depression, fatigue, insomnia, sweating, and pain have been reported during taper or after discontinuation of dopamine agonists, including pramipexole dihydrochloride extended-release tablets. These symptoms generally do not respond to levodopa.

Prior to discontinuation of pramipexole dihydrochloride extended-release tablets, patients should be informed about potential withdrawal symptoms, and monitored during and after discontinuation. In case of severe withdrawal symptoms, a trial re-administration of a dopamine agonist at the lowest effective dose may be considered.

6 ADVERSE REACTIONS

The following adverse reactions are discussed in greater detail in other sections of the labeling:

- Falling Asleep During Activities of Daily Living and Somnolence [see Warnings and Precautions (5.1) ]
- Symptomatic Orthostatic Hypotension [see Warnings and Precautions (5.2) ]
- Impulse Control/Compulsive Behaviors [see Warnings and Precautions (5.3) ]
- Hallucinations and Psychotic-like Behavior [see Warnings and Precautions (5.4) ]
- Dyskinesia [see Warnings and Precautions (5.5) ]
- Postural Deformity [see Warnings and Precautions (5.6) ]
- Rhabdomyolysis [see Warnings and Precautions (5.8) ]
- Retinal Pathology [see Warnings and Precautions (5.9) ]
- Events Reported with Dopaminergic Therapy [see Warnings and Precautions (5.10) ]
- Withdrawal Symptoms [see Warnings and Precautions (5.11) ]

6.1 Clinical Trials Experience

Because clinical trials are conducted under widely varying conditions, adverse reaction rates observed in the clinical trials of a drug cannot be directly compared to rates in the clinical trials of another drug (or of another development program of a different formulation of the same drug) and may not reflect the rates observed in practice.

During the premarketing development of pramipexole dihydrochloride extended-release tablets, patients with early Parkinson's disease were treated with pramipexole dihydrochloride extended-release tablets, placebo, or immediate-release pramipexole tablets. In addition, a randomized, double-blind, parallel group trial was conducted in 156 early Parkinson's disease patients (Hoehn & Yahr Stages I-III) to assess overnight switching of immediate-release pramipexole tablets to pramipexole dihydrochloride extended-release tablets. In this latter study, concomitant treatment with stable doses of levodopa, monoamine oxidase B inhibitor (MAOB-I) drugs, anticholinergics, or amantadine, individually or in combination, was allowed. In a third trial, advanced Parkinson's disease patients received pramipexole dihydrochloride extended-release tablets, placebo, or immediate-release pramipexole tablets as adjunctive therapy to levodopa.

Early Parkinson's Disease

The most common adverse reactions (≥5% and more frequent than placebo) after 33 weeks of treatment with pramipexole dihydrochloride extended-release tablets in the trial of early Parkinson's disease patients were somnolence, nausea, constipation, dizziness, fatigue, hallucinations, dry mouth, muscle spasms, and peripheral edema.

Twenty four of 223 (11%) patients treated with pramipexole dihydrochloride extended-release tablets for 33 weeks discontinued treatment due to adverse reactions compared to 4 of 103 (4%) patients who received placebo and approximately 20 of 213 (9%) patients who received immediate-release pramipexole tablets. The adverse reaction most commonly causing discontinuation of treatment with pramipexole dihydrochloride extended-release tablets was nausea (2%).

Table 1 lists adverse reactions that occurred with a frequency of at least 2% with pramipexole dihydrochloride extended-release tablets and were more frequent than with placebo during 33 weeks of treatment in a double-blind, placebo-controlled study in early Parkinson's disease. In this study, patients did not receive concomitant levodopa; however, levodopa was permitted as rescue medication.

Table 1 Adverse-Reactions in a 33-Week Double-Blind, Placebo-Controlled Trial with Pramipexole Dihydrochloride Extended-Release Tablets in Early Parkinson's Disease

Body System/Adverse Reaction | Placebo | Pramipexole Dihydrochloride Extended- Release Tablets | Immediate-Release Pramipexole
 | (n=103) | (n=223) | (n=213)
 | % | % | %
Nervous system disorders
Somnolence | 15 | 36 | 33
Dizziness | 7 | 12 | 12
Tremor | 1 | 3 | 3
Balance disorder | 1 | 2 | 0
Gastrointestinal disorders
Nausea | 9 | 22 | 24
Constipation | 2 | 14 | 12
Dry mouth | 1 | 5 | 4
Vomiting | 0 | 4 | 4
Upper abdominal pain | 1 | 3 | 4
Dyspepsia | 2 | 3 | 3
Abdominal discomfort | 0 | 2 | 1
Psychiatric disorders
Hallucinations, including visual, auditory and mixed | 1 | 5 | 6
Insomnia | 3 | 4 | 4
Sleep attacks or sudden onset of sleep | 1 | 3 | 6
Sleep disorder | 1 | 2 | 3
Depression | 0 | 2 | 0
General disorders and administration site conditions
Fatigue | 4 | 6 | 6
Peripheral edema | 4 | 5 | 8
Asthenia | 2 | 3 | 1
Musculoskeletal and connective tissue disorders
Muscle spasms | 3 | 5 | 3
Injury, poisoning and procedural complications
Fall | 1 | 4 | 4
Ear and labyrinth disorders
Vertigo | 1 | 4 | 2
Respiratory, thoracic and mediastinal disorders
Cough | 1 | 3 | 3
Metabolism and nutrition disorders
Increased appetite | 1 | 3 | 2
Vascular disorders
Orthostatic hypotension | 1 | 3 | 0

Because this study used a flexible dose titration design, it was not possible to assess the effects of dose on the incidence of adverse reactions.

Adverse reactions can initially occur in either the titration or maintenance phase. Some adverse reactions developed in pramipexole dihydrochloride extended-release tablets -treated patients during the titration phase and persisted (≥7 days) into the maintenance phase (i.e., pramipexole dihydrochloride extended-release tablets % - placebo % = treatment difference ≥2%); persistent adverse reactions were somnolence, nausea, constipation, fatigue, and dry mouth.

A double-blind, randomized, parallel group trial evaluated the tolerability of an overnight switch from immediate-release pramipexole tablets to pramipexole dihydrochloride extended-release tablets at the same daily dose in 156 early Parkinson's disease patients with or without levodopa. One of 104 patients switched from immediate-release pramipexole tablets to pramipexole dihydrochloride extended-release tablets discontinued due to adverse reactions (vertigo and nausea).

Advanced Parkinson's Disease

The most common adverse reactions (≥5% and greater frequency than in placebo) during 18 weeks of treatment with pramipexole dihydrochloride extended-release tablets in the trial of advanced Parkinson's disease patients with concomitant levodopa were dyskinesia, nausea, constipation, hallucinations, headache, and anorexia.

Eight of 164 (5%) patients treated with pramipexole dihydrochloride extended-release tablets for 18 weeks discontinued treatment due to adverse reactions compared to 7 of 178 (4%) patients who received placebo and 8 of 175 (5%) patients who received immediate-release pramipexole tablets. The most common adverse reactions leading to discontinuation of treatment with pramipexole dihydrochloride extended-release tablets were nausea (1%) and hallucination (1%).

Table 2 lists adverse reactions that occurred with a frequency of at least 2% with pramipexole dihydrochloride extended-release tablets and were more frequent than with placebo during 18 weeks of treatment in patients with advanced Parkinson's disease treated with pramipexole dihydrochloride extended-release tablets. In this study, pramipexole dihydrochloride extended-release tablets, immediate-release pramipexole tablets, or placebo was administered to patients who were also receiving concomitant levodopa.

Table 2 Adverse-Reactions in an 18-Week Double-Blind, Placebo-Controlled Trial with Pramipexole Dihydrochloride Extended-Release Tablets in Advanced Parkinson's Disease

Body System/Adverse Reaction | Placebo | Pramipexole Dihydrochloride Extended-Release Tablets | Immediate-Release Pramipexole
 | n=178 | n=164 | n=175
 | % | % | %
Nervous system disorders
Dyskinesia | 8 | 17 | 18
Headache | 3 | 7 | 4
Dizziness (postural) | 1 | 2 | 3
Gastrointestinal disorders
Nausea | 10 | 11 | 11
Constipation | 5 | 7 | 6
Salivary hypersecretion | 0 | 2 | 0
Diarrhea | 1 | 2 | 1
Psychiatric disorders
Hallucinations, including visual, auditory and mixed | 2 | 9 | 7
Insomnia | 2 | 4 | 4
Metabolism and nutrition disorders
Anorexia | 2 | 5 | 1
Musculoskeletal and connective tissue disorders
Back pain | 1 | 2 | 3

Because this flexible dose study used a titration design, it was not possible to assess the effects of dose on the incidence of adverse reactions.

Adverse reactions can initially occur in either the titration or maintenance phase. Some adverse reactions developed in pramipexole dihydrochloride extended-release tablets -treated patients during the titration phase and persisted (≥7 days) into the maintenance phase (i.e., pramipexole dihydrochloride extended-release tablets % - placebo % = treatment difference ≥2%); persistent adverse reactions were dyskinesia and insomnia.

Laboratory Tests

During the development of pramipexole dihydrochloride extended-release tablets, no systematic abnormalities on routine laboratory testing were noted.

Other adverse reactions observed during clinical trials of pramipexole dihydrochloride immediate-release or pramipexole dihydrochloride extended-release tablets in early and advanced Parkinson's disease

Other adverse reactions in clinical studies involving pramipexole dihydrochloride immediate-release or pramipexole dihydrochloride extended-release tablets include abnormal dreams, akathisia, amnesia, decreased libido, decreased weight, dyspnea, pneumonia, and vision abnormalities.

6.2 Postmarketing Experience

The following adverse reactions have been identified during postapproval use of pramipexole dihydrochloride immediate-release or pramipexole dihydrochloride extended-release tablets, primarily in Parkinson's disease patients. Because these reactions are reported voluntarily from a population of uncertain size, it is not always possible to reliably estimate their frequency or establish a causal relationship to drug exposure. Decisions to include these reactions in labeling are typically based on one or more of the following factors: (1) seriousness of the reaction, (2) frequency of reporting, or (3) strength of causal connection to pramipexole tablets.

Cardiac Disorders: cardiac failure

Gastrointestinal Disorders: vomiting

General Disorders and Administration Site Conditions: withdrawal symptoms [see Warnings and Precautions (5.11)]

Metabolism and Nutrition Disorders: syndrome of inappropriate antidiuretic hormone secretion (SIADH), weight increase

Musculoskeletal and Connective Tissue Disorders: postural deformity [see Warnings and Precautions (5.6)]

Nervous System Disorders: syncope

Reproductive System and Breast Disorders: priapism

Skin and Subcutaneous Tissue Disorders: skin reactions (including erythema, rash, pruritus, urticaria)

There are postmarketing reports of patients noticing tablet residue in their stool that resembles a swollen pramipexole dihydrochloride extended-release whole tablet or swollen pieces of the tablet. Some patients have reported worsening of their Parkinson's disease symptoms when tablet residue was observed. If a patient reports tablet residue with worsening of their Parkinson's symptoms, prescribers may need to re-evaluate their medications.

7 DRUG INTERACTIONS

7.1 Dopamine Antagonists

Since pramipexole is a dopamine agonist, it is possible that dopamine antagonists, such as the neuroleptics (phenothiazines, butyrophenones, thioxanthenes) or metoclopramide, may diminish the effectiveness of pramipexole dihydrochloride extended-release tablets.

8 USE IN SPECIFIC POPULATIONS

8.1 Pregnancy

Risk Summary

There are no adequate data on the developmental risk associated with the use of pramipexole dihydrochloride extended-release tablets in pregnant women. No adverse developmental effects were observed in animal studies in which pramipexole was administered to rabbits during pregnancy. Effects on embryofetal development could not be adequately assessed in pregnant rats; however, postnatal growth was inhibited at clinically relevant exposures [see Data].

In the U.S. general population, the estimated background risk of major birth defects and of miscarriage in clinically recognized pregnancies is 2% to 4% and 15% to 20%, respectively. The background risk of major birth defects and miscarriage for the indicated population is unknown.

Data

Animal Data

Oral administration of pramipexole (0.1, 0.5, or 1.5 mg/kg/day) to pregnant rats during the period of organogenesis resulted in a high incidence of total resorption of embryos at the highest dose tested. This increase in embryolethality is thought to result from the prolactin-lowering effect of pramipexole; prolactin is necessary for implantation and maintenance of early pregnancy in rats but not in rabbits or humans. Because of pregnancy disruption and early embryonic loss in this study, the teratogenic potential of pramipexole could not be adequately assessed in rats. The highest no-effect dose for embryolethality in rats was associated with maternal plasma drug exposures (AUC) approximately equal to those in humans receiving the maximum recommended human dose (MRHD) of 4.5 mg/day. There were no adverse effects on embryo-fetal development following oral administration of pramipexole (0.1, 1, or 10 mg/kg/day) to pregnant rabbits during organogenesis (plasma AUC up to approximately 70 times that in humans at the MRHD). Postnatal growth was inhibited in the offspring of rats treated with pramipexole (0.1, 0.5, or 1.5 mg/kg/day) during the latter part of pregnancy and throughout lactation. The no-effect dose for adverse effects on offspring growth (0.1 mg/kg/day) was associated with maternal plasma drug exposures lower than that in humans at the MRHD.

8.2 Lactation

Risk Summary

There are no data on the presence of pramipexole in human milk, the effects of pramipexole on the breastfed infant, or the effects of pramipexole on milk production. However, inhibition of lactation is expected because pramipexole inhibits secretion of prolactin in humans. Pramipexole or metabolites, or both, are present in rat milk [see Data].

The developmental and health benefits of breastfeeding should be considered along with the mother's clinical need for pramipexole dihydrochloride extended-release tablets and any potential adverse effects on the breastfed infant from pramipexole dihydrochloride extended-release tablets or from the underlying maternal condition.

Data

In a study of radio-labeled pramipexole, pramipexole or metabolites, or both, were present in rat milk at concentrations three to six times higher than those in maternal plasma.

8.4 Pediatric Use

Safety and effectiveness of pramipexole dihydrochloride extended-release tablets in pediatric patients have not been evaluated.

8.5 Geriatric Use

Pramipexole total oral clearance is approximately 30% lower in subjects older than 65 years compared with younger subjects, because of a decline in pramipexole renal clearance due to an age-related reduction in renal function. This resulted in an increase in elimination half-life from approximately 8.5 hours to 12 hours. In a placebo-controlled clinical trial of pramipexole dihydrochloride extended-release tablets in early Parkinson's disease, 47% of the 259 patients were ≥65 years of age. Among patients receiving pramipexole dihydrochloride extended-release tablets, hallucinations were more common in the elderly, occurring in 13% of the patients ≥65 years of age compared to 2% of the patients <65 years of age.

8.6 Renal Impairment

The elimination of pramipexole is dependent upon renal function. Pramipexole clearance is extremely low in dialysis patients, as a negligible amount of pramipexole is removed by dialysis [see Dosage and Administration (2.2), Warnings and Precautions (5.7), and Clinical Pharmacology (12.3)].

10 OVERDOSAGE

There is no clinical experience with significant overdosage. One patient took 11 mg/day of pramipexole for 2 days in a clinical trial for an investigational use. Blood pressure remained stable, although pulse rate increased to between 100 and 120 beats/minute. No other adverse reactions were reported related to the increased dose.

There is no known antidote for overdosage of a dopamine agonist. If signs of central nervous system stimulation are present, a phenothiazine or other butyrophenone neuroleptic agent may be indicated; the efficacy of such drugs in reversing the effects of overdosage has not been assessed. Management of overdose may require general supportive measures along with gastric lavage, intravenous fluids, and electrocardiogram monitoring.

11 DESCRIPTION

Pramipexole dihydrochloride extended-release tablets contain pramipexole dihydrochloride (as a monohydrate). Pramipexole is a non-ergot dopamine agonist. The chemical name of pramipexole dihydrochloride monohydrate is (S)-2-amino-4,5,6,7- tetrahydro-6-(propylamino)benzothiazole dihydrochloride monohydrate. Its empirical formula is C10 H17 N3 S · 2HCl · H2O, and its molecular weight is 302.26.

The structural formula is:

Pramipexole dihydrochloride is a white to off-white powder substance. Melting occurs in the range of 296°C to 301°C, with decomposition. Pramipexole dihydrochloride is more than 20% soluble in water, about 8% in methanol, about 0.5% in ethanol, and practically insoluble in dichloromethane.

Pramipexole dihydrochloride extended-release tablets 0.375 mg:

Each extended-release tablet contains 0.375 mg pramipexole dihydrochloride monohydrate equivalent to 0.352 mg pramipexole dihydrochloride.

Pramipexole dihydrochloride extended-release tablets 0.75 mg:

Each extended-release tablet contains 0.75 mg pramipexole dihydrochloride monohydrate equivalent to 0.705 mg pramipexole dihydrochloride.

Pramipexole dihydrochloride extended-release tablets 1.5 mg:

Each extended-release tablet contains 1.5 mg pramipexole dihydrochloride monohydrate equivalent to 1.41 mg pramipexole dihydrochloride.

Pramipexole dihydrochloride extended-release tablets 2.25 mg:

Each extended-release tablet contains 2.25 mg pramipexole dihydrochloride monohydrate equivalent to 2.12 mg pramipexole dihydrochloride.

Pramipexole dihydrochloride extended-release tablets 3 mg:

Each extended-release tablet contains 3 mg pramipexole dihydrochloride monohydrate equivalent to 2.82 mg pramipexole dihydrochloride.

Pramipexole dihydrochloride extended-release tablets 3.75 mg:

Each extended-release tablet contains 3.75 mg pramipexole dihydrochloride monohydrate equivalent to 3.53 mg pramipexole dihydrochloride.

Pramipexole dihydrochloride extended-release tablets 4.5 mg:

Each extended-release tablet contains 4.5 mg pramipexole dihydrochloride monohydrate equivalent to 4.23 mg pramipexole dihydrochloride.

Inactive ingredients for all strengths of Pramipexole dihydrochloride extended-release tablets consist of hypromellose, corn starch, microcrystalline cellulose, sodium lauryl sulfate, sodium metabisulfite and magnesium stearate.

12 CLINICAL PHARMACOLOGY

12.1 Mechanism of Action

Pramipexole is a non-ergot dopamine agonist with high relative in vitro specificity and full intrinsic activity at the D2 subfamily of dopamine receptors, binding with higher affinity to D3 than to D2 or D4 receptor subtypes.

The precise mechanism of action of pramipexole as a treatment for Parkinson's disease is unknown, although it is believed to be related to its ability to stimulate dopamine receptors in the striatum. This conclusion is supported by electrophysiologic studies in animals that have demonstrated that pramipexole influences striatal neuronal firing rates via activation of dopamine receptors in the striatum and the substantia nigra, the site of neurons that send projections to the striatum. The relevance of D3 receptor binding in Parkinson's disease is unknown.

12.2 Pharmacodynamics

The effect of pramipexole on the QT interval of the ECG was investigated in a clinical study in 60 healthy male and female volunteers. All subjects initiated treatment with 0.375 mg pramipexole dihydrochloride extended-release tablets administered once daily, and were up-titrated every 3 days to 2.25 mg and 4.5 mg daily, a faster rate of titration than recommended in the label. No dose- or exposure-related effect on mean QT intervals was observed; however, the study did not have a valid assessment of assay sensitivity. The effect of pramipexole on QTc intervals at higher exposures achieved either due to drug interactions (e.g., with cimetidine), renal impairment, or at higher doses has not been systematically evaluated.

Although mean values remained within normal reference ranges throughout the study, supine systolic blood pressure (SBP), diastolic blood pressure (DBP), and pulse rate for subjects treated with pramipexole generally increased during the rapid up-titration phase, by 10 mmHg, 7 mmHg, and 10 bpm higher than placebo, respectively. Higher SBP, DBP, and pulse rates compared to placebo were maintained until the pramipexole doses were tapered; values on the last day of tapering were generally similar to baseline values. Such effects have not been observed in clinical studies with Parkinson's disease patients, who were titrated according to labeled recommendations.

12.3 Pharmacokinetics

Pramipexole dihydrochloride extended- release tablets, like immediate-release pramipexole tablets, display linear pharmacokinetics over the entire clinical dosage range. Slow release of pramipexole from pramipexole dihydrochloride extended- release tablets with once-daily administration results in the same daily maximum and minimum pramipexole plasma concentrations (Cmax, Cmin) as three times daily administration of immediate-release pramipexole tablets.

Absorption

The absolute bioavailability of pramipexole is greater than 90%, indicating that it is well absorbed and undergoes little presystemic metabolism.

Increase in systemic exposure of pramipexole following oral administration of 0.375 mg to 4.5 mg of pramipexole dihydrochloride extended- release tablets was dose-proportional. For pramipexole dihydrochloride extended-release tablets, steady state of exposure is reached within 5 days of continuous dosing.

Relative bioavailability of pramipexole dihydrochloride extended- release tablets compared with immediate-release tablets was approximately 100%. In a repeat-dose study in healthy, normal volunteers, pramipexole dihydrochloride extended- release tablets 4.5 mg administered once daily was bioequivalent with regard to Cmax and AUC over 24 hours to immediate-release pramipexole tablets 1.5 mg administered three times daily. The average time-to-peak concentration for pramipexole dihydrochloride extended-release tablets is 6 hours. Administration of pramipexole dihydrochloride extended- release tablets with food (i.e., high-fat meal) did not affect AUC but increased Cmax by approximately 20% and delayed Tmax by approximately 2 hours compared with dosing under fasted conditions; these differences are not considered to be clinically relevant [see Dosage and Administration (2.1)].

Distribution

Pramipexole is extensively distributed, having a volume of distribution of about 500 L (coefficient of variation [CV] = 20%). It is about 15% bound to plasma proteins. Pramipexole distributes into red blood cells as indicated by an erythrocyte-to-plasma ratio of approximately 2.

Metabolism

Pramipexole is metabolized only to a negligible extent (<10%). No specific active metabolite has been identified in human plasma or urine.

Elimination

Urinary excretion is the major route of pramipexole elimination, with 90% of a pramipexole dose recovered in urine, almost all as unchanged drug. The renal clearance of pramipexole is approximately 400 mL/min (CV=25%), approximately three times higher than the glomerular filtration rate. Thus, pramipexole is secreted by the renal tubules, probably by the organic cation transport system.

Pharmacokinetics in Specific Populations

Because therapy with pramipexole dihydrochloride extended-release tablets is initiated at a low dose and gradually titrated upward according to clinical tolerability to obtain the optimum therapeutic effect, adjustment of the initial dose based on gender, weight, race, or age is not necessary. However, renal insufficiency causes a large decrease in the ability to eliminate pramipexole. This will necessitate dosage adjustment in patients with moderate to severe renal impairment [see Dosage and Administration (2.2)].

Gender

Pramipexole clearance is about 30% lower in women than in men, but this difference can be accounted for by differences in body weight. There is no difference in plasma half-life between males and females.

Age

Pramipexole clearance is reduced by approximately 30% in the elderly (aged 65 years or older) compared with young, healthy volunteers (aged less than 40 years). This difference is most likely due to the reduction in renal function with age, since pramipexole clearance is correlated with renal function, as measured by creatinine clearance.

Race

No racial differences in metabolism and elimination have been identified.

Hepatic Impairment

The influence of hepatic insufficiency on pramipexole pharmacokinetics has not been evaluated. Because approximately 90% of the recovered dose is excreted in the urine as unchanged drug, hepatic impairment would not be expected to have a significant effect on pramipexole elimination.

Renal Impairment

Clearance of immediate-release pramipexole was about 75% lower in patients with severe renal impairment (creatinine clearance approximately 20 mL/min) and about 60% lower in patients with moderate impairment (creatinine clearance approximately 40 mL/min) compared with healthy volunteers [see Dosage and Administration (2.2) and Warnings and Precautions (5.7)]. In patients with varying degrees of renal impairment, pramipexole clearance correlates well with creatinine clearance. Therefore, creatinine clearance can be used as a predictor of the extent of decrease in pramipexole clearance.

Drug Interactions

No specific pharmacokinetic drug interaction trials were conducted with pramipexole dihydrochloride extended-release tablets since the potential for drug interactions mainly depends on the active drug substance pramipexole and not the formulation. The following interaction data were obtained using immediate-release pramipexole tablets.

Carbidopa/levodopa: Carbidopa/levodopa did not influence the pharmacokinetics of pramipexole in healthy volunteers (N=10). Pramipexole did not alter the extent of absorption (AUC) or the elimination of carbidopa/levodopa, although it caused an increase in levodopa Cmax by about 40% and a decrease in Tmax from 2.5 to 0.5 hours.

Selegiline: In healthy volunteers (N=11), selegiline did not influence the pharmacokinetics of pramipexole.

Amantadine: Population pharmacokinetic analyses suggest that amantadine may slightly decrease the oral clearance of pramipexole.

Cimetidine: Cimetidine, a known inhibitor of renal tubular secretion of organic bases via the cationic transport system, caused a 50% increase in pramipexole AUC and a 40% increase in half-life (N=12).

Probenecid: Probenecid, a known inhibitor of renal tubular secretion of organic acids via the anionic transporter, did not noticeably influence pramipexole pharmacokinetics (N=12).

Other drugs eliminated via renal secretion: Population pharmacokinetic analysis suggests that co- administration of drugs that are secreted by the cationic transport system (e.g., cimetidine, ranitidine, diltiazem, triamterene, verapamil, quinidine, and quinine) decreases the oral clearance of pramipexole by about 20%, while those secreted by the anionic transport system (e.g., cephalosporins, penicillins, indomethacin, hydrochlorothiazide, and chlorpropamide) are likely to have little effect on the oral clearance of pramipexole. Other known organic cation transport substrates and/or inhibitors (e.g., cisplatin and procainamide) may also decrease the clearance of pramipexole.

CYP interactions: Inhibitors of cytochrome P450 enzymes would not be expected to affect pramipexole elimination because pramipexole is not appreciably metabolized by these enzymes in vivo or in vitro. Pramipexole does not inhibit CYP enzymes CYP1A2, CYP2C9, CYP2C19, CYP2E1, and CYP3A4. Inhibition of CYP2D6 was observed with an apparent Ki of 30 µM, indicating that pramipexole will not inhibit CYP enzymes at plasma concentrations observed following the clinical dose of 4.5 mg/day.

Drugs affecting gastrointestinal motility or gastric pH: Population pharmacokinetic analysis suggests that co-administration of antacids (N=6) decreased the oral clearance of pramipexole by about 25%, while H2-blockers (N=5), anticholinergics (N=27), propulsive (N=7), and proton pump inhibitors (N=16) are likely to have little effect on the oral clearance of pramipexole.

13 NONCLINICAL TOXICOLOGY

13.1 Carcinogenesis, Mutagenesis, Impairment of Fertility

Two-year carcinogenicity studies with pramipexole have been conducted in mice and rats. Pramipexole was administered in the diet to mice at doses up to 10 mg/kg/day [or approximately 10 times the maximum recommended human dose (MRHD) of 1.5 mg TID on a mg/m^2 basis]. Pramipexole was administered in the diet to rats at doses up to 8 mg/kg/day. These doses were associated with plasma AUCs up to approximately 12 times that in humans at the MRHD. No significant increases in tumors occurred in either species.

Pramipexole was not mutagenic or clastogenic in a battery of in vitro (bacterial reverse mutation, V79/HGPRT gene mutation, chromosomal aberration in CHO cells) and in vivo (mouse micronucleus) assays.

In rat fertility studies, pramipexole at a dose of 2.5 mg/kg/day (5 times the MRHD on a mg/m^2 basis) prolonged estrus cycles and inhibited implantation. These effects were associated with reductions in serum levels of prolactin, a hormone necessary for implantation and maintenance of early pregnancy in rats.

13.2 Animal Toxicology and/or Pharmacology

Retinal Pathology in Albino Rats

Pathologic changes (degeneration and loss of photoreceptor cells) were observed in the retina of albino rats in the 2-year carcinogenicity study with pramipexole. These findings were first observed during week 76 and were dose-dependent in animals receiving 2 or 8 mg/kg/day (plasma AUCs equal to 2.5 and 12.5 times that in humans at the MRHD of 1.5 mg TID). In a similar study of pigmented rats with 2-years exposure to pramipexole at 2 or 8 mg/kg/day, retinal degeneration was not observed. Animals given drug had thinning in the outer nuclear layer of the retina that was only slightly greater than that seen in control rats.

Investigative studies demonstrated that pramipexole reduced the rate of disk shedding from the photoreceptor rod cells of the retina in albino rats, which was associated with enhanced sensitivity to the damaging effects of light. In a comparative study, degeneration and loss of photoreceptor cells occurred in albino rats after 13 weeks of treatment with 25 mg/kg/day of pramipexole (54 times the highest clinical dose on a mg/m^2 basis) and constant light (100 lux), but not in pigmented rats exposed to the same dose and higher light intensities (500 lux). Thus, the retina of albino rats is considered to be uniquely sensitive to the damaging effects of pramipexole and light. Similar changes in the retina did not occur in a 2-year carcinogenicity study in albino mice treated with 0.3, 2, or 10 mg/kg/day (0.3, 2.2, and 11 times the highest clinical dose on a mg/m^2 basis).

Evaluation of the retinas of monkeys given 0.1, 0.5, or 2.0 mg/kg/day of pramipexole (0.4, 2.2, and 8.6 times the highest clinical dose on a mg/m^2 basis) for 12 months and minipigs given 0.3, 1, or 5 mg/kg/day of pramipexole for 13 weeks also detected no changes.

The potential significance of this effect in humans has not been established, but cannot be disregarded because disruption of a mechanism that is universally present in vertebrates (i.e., disk shedding) may be involved.

Fibro-osseous Proliferative Lesions in Mice

An increased incidence of fibro-osseous proliferative lesions occurred in the femurs of female mice treated for 2 years with 0.3, 2.0, or 10 mg/kg/day (0.3, 2.2, and 11 times the highest clinical dose on a mg/m^2 basis). Lesions occurred at a lower rate in control animals. Similar lesions were not observed in male mice or rats and monkeys of either sex that were treated chronically with pramipexole. The significance of this lesion to humans is not known.

14 CLINICAL STUDIES

The effectiveness of pramipexole dihydrochloride extended- release tablets in the treatment of Parkinson's disease was supported by clinical pharmacokinetic data [see Clinical Pharmacology (12.3)] and two randomized, double-blind, placebo- controlled, multicenter clinical trials in early and advanced Parkinson's disease. In both randomized studies, the Unified Parkinson's Disease Rating Scale (UPDRS) served as a primary outcome assessment measure. The UPDRS is a four-part multi-item rating scale intended to evaluate mentation (Part I), activities of daily living (Part II), motor performance (Part III), and complications of therapy (Part IV).

Part II of the UPDRS contains 13 questions related to activities of daily living, which are scored from 0 (normal) to 4 (maximal severity) for a maximum (worst) score of 52. Part III of the UPDRS contains 14 items designed to assess the severity of the cardinal motor findings in patients with Parkinson's disease (e.g., tremor, rigidity, bradykinesia, postural instability, etc.), scored for different body regions and has a maximum (worst) score of 108.

Early Parkinson's Disease

The effectiveness of pramipexole dihydrochloride extended- release tablets in early Parkinson's disease patients (Hoehn & Yahr Stages I-III) who were not on levodopa therapy was established in a randomized, double-blind, placebo-controlled, 3- parallel-group clinical study. Patients were treated with pramipexole dihydrochloride extended-release tablets, immediate-release pramipexole tablets, or placebo; those treated with pramipexole dihydrochloride extended-release tablets or immediate-release pramipexole tablets had a starting dose of 0.375 mg/day followed by a flexible up-titration, based on efficacy and tolerability, up to 4.5 mg/day. Levodopa was permitted during the study as rescue medication. Stable doses of concomitant MAO-B inhibitors, anticholinergics, or amantadine, individually or in combination, were allowed. The primary efficacy endpoint was the mean change from baseline in the UPDRS Parts II+III score for pramipexole dihydrochloride extended-release tablets versus placebo following 18 weeks of treatment.

At 18 weeks of treatment, the mean change from baseline UPDRS Parts II+III score was –8.1 points in patients receiving pramipexole dihydrochloride extended- release tablets (n=102) and –5.1 points in patients receiving placebo (n=50), a difference that was statistically significant (p<0.03). Seven patients treated with placebo (14%) and 3 patients treated with pramipexole dihydrochloride extended-release tablets (3%) received levodopa rescue medication. At 18 weeks, the mean dose of pramipexole dihydrochloride extended- release tablets was 3 mg/day.

At 33-weeks, the adjusted mean improvement from baseline UPDRS Parts II+III score was –8.6 points in patients receiving pramipexole dihydrochloride extended- release tablets (n=213), compared to –3.8 points in patients receiving placebo (n=103).

At 18 and 33 weeks, the mean dose of pramipexole dihydrochloride extended- release tablets was approximately 3 mg/day. Twenty-two patients treated with placebo (21%) and 15 patients treated with pramipexole dihydrochloride extended-release tablets (7%) received levodopa rescue medication before the final assessment.

No differences in effectiveness based on age or gender were detected. Patients receiving MAOB-I, anticholinergics, or amantadine had responses similar to patients not receiving these drugs.

Advanced Parkinson's Disease

The effectiveness of pramipexole dihydrochloride extended- release tablets in advanced Parkinson's disease patients (Hoehn & Yahr Stages II- IV at "on" time) who were on concomitant levodopa therapy (at an optimized dose) and who had motor fluctuations (at least 2 cumulative hours of "off" time per day) was established in a randomized, double-blind, placebo-controlled, 3-parallel-group clinical study. Patients were treated with pramipexole dihydrochloride extended- release tablets, immediate-release pramipexole tablets, or placebo; those treated with pramipexole dihydrochloride extended-release tablets or immediate- release pramipexole tablets had a starting dose of 0.375 mg/day followed by a flexible up-titration over 7 weeks, based on efficacy and tolerability, up to 4.5 mg/day, followed by a 26 week maintenance period.

Levodopa dosage reduction was permitted only in the case of dopaminergic adverse events. The primary efficacy endpoint was the adjusted mean change from baseline in the UPDRS Parts II+III score for pramipexole dihydrochloride extended- release tablets versus placebo following 18 weeks of treatment.

At 18 weeks of treatment, the adjusted mean improvement from baseline UPDRS Parts II+III score was –11.0 points in patients receiving pramipexole dihydrochloride extended- release tablets (n=161) and –6.1 points in patients receiving placebo (n=174), (p=0.0001). At week 18, the adjusted mean improvement from baseline in "off" time was –2.1 hours for pramipexole dihydrochloride extended- release tablets and –1.4 hours for placebo (p=0.0199).

At 33-weeks the adjusted mean improvement from baseline UPDRS Parts II+III score was –11.1 points in patients receiving pramipexole dihydrochloride extended- release tablets (n=117) and –6.8 points in patients receiving placebo (n=136) (p=0.0135).

At both 18 and 33 weeks the mean daily dose of pramipexole dihydrochloride extended- release tablets was 2.6 mg/day. At week 18, 4 patients (3%) in the placebo group and 14 patients (11%) in the pramipexole dihydrochloride extended- release tablets group had decreased their levodopa daily dose compared to baseline due to dopaminergic adverse events. No clinically relevant difference in effectiveness was observed in the sub-group analyses based on gender, age, race (White vs Asian), or concomitant use of antiparkinsonian treatment (MAOB-I, amantadine or anticholinergics).

16 HOW SUPPLIED/STORAGE AND HANDLING

16.1 How Supplied

Pramipexole dihydrochloride extended- release tablets are available as follows:

0.375 mg: white or off-white, round, biconvex tablets debossed "0.375" on one side and "P11" on the other side.

Unit of Use Bottles of 30 NDC 50742-331-30

0.75 mg: white or off-white, round, biconvex tablets debossed "0.75" on one side and "P12" on the other side.

Unit of Use Bottles of 30 NDC 50742-332-30

1.5 mg: white or off-white, oval, biconvex tablets debossed "1.5" on one side and "P13" on the other side.

Unit of Use Bottles of 30 NDC 50742-333-30

2.25 mg: white or off-white, oval, biconvex tablets debossed "2.25" on one side and "P14" on the other side.

Unit of Use Bottles of 30 NDC 50742-334-30

3 mg: white or off-white, oval, biconvex tablets debossed "3.0" on one side and "P15" on the other side.

Unit of Use Bottles of 30 NDC 50742-335-30

3.75 mg: white or off-white, oval, biconvex tablets debossed "3.75" on one side and "P16" on the other side.

Unit of Use Bottles of 30 NDC 50742-336-30

4.5 mg: white or off-white, oval, biconvex tablets debossed "4.5" on one side and "P17" on the other side.

Unit of Use Bottles of 30 NDC 50742-337-30

16.2 Storage and Handling

Store at 20° to 25°C (68° to 77°F); excursions permitted to 15° to 30°C (59° to 86°F) [see USP Controlled Room Temperature]. Protect from exposure to high humidity. Store in a safe place out of the reach of children.

17 PATIENT COUNSELING INFORMATION

Advise the patient to read the FDA-approved patient labeling (Patient Information).

Dosing Instructions

Instruct patients to take pramipexole dihydrochloride extended-release tablets only as prescribed. If a dose is missed, pramipexole dihydrochloride extended-release tablets should be taken as soon as possible, but no later than 12 hours after the regularly scheduled time. After 12 hours, the missed dose should be skipped and the next dose should be taken on the following day at the regularly scheduled time.

Pramipexole dihydrochloride extended-release tablets can be taken with or without food. If patients develop nausea, advise that taking pramipexole dihydrochloride extended-release tablets with food may reduce the occurrence of nausea.

Pramipexole dihydrochloride extended-release tablets should be swallowed whole. They should not be chewed, crushed, or divided [see Dosage and Administration (2.1)].

Inform patients that residue in stool which may resemble a swollen original pramipexole dihydrochloride extended-release tablets or swollen pieces of the original tablet have been reported [see Adverse Reactions (6.2)]. Instruct patients to contact their physician if this occurs.

Pramipexole is the active ingredient that is in both pramipexole dihydrochloride extended-release tablets and immediate-release pramipexole tablets. Ensure that patients do not take both immediate-release pramipexole and pramipexole dihydrochloride extended-release tablets.

Sedating Effects

Alert patients to the potential sedating effects of pramipexole dihydrochloride extended-release tablets, including somnolence and the possibility of falling asleep while engaged in activities of daily living. Since somnolence is a frequent adverse reaction with potentially serious consequences, patients should neither drive a car nor engage in other potentially dangerous activities until they have gained sufficient experience with pramipexole dihydrochloride extended-release tablets to gauge whether or not it affects their mental and/or motor performance adversely. Advise patients that if increased somnolence or new episodes of falling asleep during activities of daily living (e.g., conversations or eating) are experienced at any time during treatment, they should not drive or participate in potentially dangerous activities until they have contacted their physician. Because of possible additive effects, advise caution when patients are taking other sedating medications or alcohol in combination with pramipexole dihydrochloride extended-release tablets and when taking concomitant medications that increase plasma levels of pramipexole (e.g., cimetidine) [see Warnings and Precautions (5.1)].

Postural (Orthostatic) Hypotension

Advise patients that they may develop postural (orthostatic) hypotension, with or without symptoms such as dizziness, nausea, fainting, or blackouts, and sometimes, sweating. Hypotension may occur more frequently during initial therapy. Accordingly, caution patients against rising rapidly after sitting or lying down, especially if they have been doing so for prolonged periods and especially at the initiation of treatment with pramipexole dihydrochloride extended-release tablets [see Warnings and Precautions (5.2)].

Impulse Control Symptoms Including Compulsive Behaviors

Alert patients and their caregivers to the possibility that they may experience intense urges to spend money, intense urges to gamble, increased sexual urges, binge eating and/or other intense urges and the inability to control these urges while taking pramipexole dihydrochloride extended-release tablets [see Warnings and Precautions (5.3)].

Hallucinations and Psychotic-like Behavior

Inform patients that hallucinations and other psychotic-like behavior can occur. In patients with Parkinson's disease, the elderly are at a higher risk than younger patients [see Warnings and Precautions (5.4)].

Withdrawal-Emergent Hyperpyrexia and Confusion

Advise patients who have been prescribed a lower dose or who have been withdrawn from the drug to notify their healthcare provider if they have symptoms such as fever, muscular rigidity or altered consciousness [see Warnings and Precautions (5.10)].

Withdrawal Symptoms

Advise patients that withdrawal symptoms may occur during or after discontinuation or dose reduction of pramipexole dihydrochloride extended-release tablets. Advise patients who have been prescribed a lower dose or who have been withdrawn from the drug to notify their healthcare provider if they have withdrawal symptoms such as apathy, anxiety, depression, fatigue, insomnia, sweating, or pain. Notify patients that in case of severe withdrawal symptoms, a trial re-administration of a dopamine agonist at the lowest effective dose may be considered [see Warnings and Precautions (5.11)].

Pregnancy

Because the teratogenic potential of pramipexole has not been completely established in laboratory animals, and because experience in humans is limited, advise women to notify their physicians if they become pregnant or intend to become pregnant during therapy [see Use in Specific Populations (8.1)].

Lactation

Because of the possibility that pramipexole may be excreted in breast milk, advise women to notify their physicians if they intend to breast-feed or are breast-feeding an infant [see Use in Specific Populations (8.2)].

I0166

Rev. B
Iss. Jul 2024

Manufactured for:

Ingenus Pharmaceuticals, LLC

Orlando, FL 32811-7193

Made in China

Patient Information

Pramipexole Dihydrochloride

(pram" i pex' ole dye hye" droe klor' ide) extended-release tablets

Read this Patient Information before you start taking pramipexole dihydrochloride extended-release tablets and each time you get a refill. There may be new information. This information does not take the place of talking with your doctor about your medical condition or your treatment.

What is pramipexole dihydrochloride extended-release tablet?

Pramipexole dihydrochloride extended- release tablet is a prescription medicine used to treat the signs and symptoms of Parkinson's disease.

It is not known if pramipexole dihydrochloride extended- release tablets are safe and effective in children.

What should I tell my doctor before taking pramipexole dihydrochloride extended- release tablets?

Before taking pramipexole dihydrochloride extended- release tablets, tell your doctor if you:

- feel sleepy during the day
- have low blood pressure, or if you feel dizzy or faint, especially when getting up from sitting or lying down.
- have trouble controlling your muscles (dyskinesia)
- have kidney problems
- drink alcohol. Alcohol can increase the chance that pramipexole dihydrochloride extended- release tablets will make you feel sleepy or fall asleep when you should be awake.
- are pregnant or plan to become pregnant. It is not known if pramipexole dihydrochloride extended- release tablets will harm your unborn baby.
- are breastfeeding or plan to breastfeed. It is not known if pramipexole dihydrochloride pass into your breast milk. You and your doctor should decide if you will take pramipexole dihydrochloride extended- release tablets or breastfeed. You should not do both.

Tell your doctor about all the medicines you take, including prescription and over-the-counter medicines, vitamins, and herbal supplements.

Pramipexole dihydrochloride extended- release tablets and other medicines may affect each other causing side effects. Pramipexole dihydrochloride extended- release tablets may affect the way other medicines work, and other medicines may affect how pramipexole dihydrochloride extended- release tablets work.

Especially tell your doctor if you take:

- medicines called neuroleptics (phenothiazines, butyrophenones, thioxanthenes) or metoclopramide. Pramipexole dihydrochloride extended- release tablets may not work as well if you take these medicines.
- pramipexole. Pramipexole is the active ingredient in pramipexole dihydrochloride extended-release tablets. If you are taking pramipexole, you should not take pramipexole dihydrochloride extended-release tablets.
- any other medicines that make you sleepy or may increase the effects of pramipexole dihydrochloride extended-release tablets, such as cimetidine (Tagamet).

Ask your doctor for a list of these medicines if you are not sure.

Know the medicines you take. Keep a list of them and show it to your doctor and pharmacist when you get a new medicine.

How should I take pramipexole dihydrochloride extended-release tablets?

- Pramipexole dihydrochloride extended-release tablets are taken once daily.
- Your doctor will tell you how much pramipexole dihydrochloride extended- release tablets to take and when to take it. Do not take more or less pramipexole dihydrochloride extended- release tablets than your doctor tells you to.
- Swallow pramipexole dihydrochloride extended- release tablets whole. Do not chew, crush, or cut pramipexole dihydrochloride extended- release tablets.
- Pramipexole dihydrochloride extended- release tablets can be taken with or without food. Taking pramipexole dihydrochloride extended- release tablets with food may lower your chances of getting nausea.
- You may see something that looks like a swollen original tablet or swollen pieces of the original tablet in your stool. If this happens, tell your doctor.
- If you miss a dose of pramipexole dihydrochloride extended- release tablets it should be taken as soon as possible, but no later than 12 hours after your regularly scheduled time. If it is later than 12 hours, the missed dose should be skipped and the next dose should be taken on the following day at your regularly scheduled time. Do not double your next pramipexole dihydrochloride extended- release tablets dose .
- Do not stop taking pramipexole dihydrochloride extended- release tablets without talking to your doctor first. If your doctor tells you to stop taking pramipexole dihydrochloride extended- release tablets, you should ask your doctor for specific instructions on how to slowly and safely discontinue taking pramipexole dihydrochloride extended- release tablets. If you stop taking pramipexole dihydrochloride extended- release tablets you may have withdrawal symptoms (see "withdrawal symptoms" under "What are the possible side effects of pramipexole dihydrochloride extended- release tablets? ").

What should I avoid while taking pramipexole dihydrochloride extended-release tablets?

- Do not drink alcohol while taking pramipexole dihydrochloride extended- release tablets. It can increase your chance of having serious side effects. See "What are the possible side effects of pramipexole dihydrochloride extended- release tablets?"
- Do not drive a car, operate a machine, or do other dangerous activities until you know how pramipexole dihydrochloride extended- release tablets affect you. Sleepiness caused by pramipexole dihydrochloride extended- release tablets can happen as late as 1 year after you start your treatment.

What are the possible side effects of pramipexole dihydrochloride extended- release tablets?

Pramipexole dihydrochloride extended- release tablets may cause serious side effects, including:

● falling asleep during normal daily activities. Pramipexole dihydrochloride extended- release tablets may cause you to fall asleep while you are doing daily activities such as driving, talking with other people, or eating.

● Some people taking the medicine in pramipexole dihydrochloride extended-release tablets have had car accidents because they fell asleep while driving.

● Some people did not feel sleepy before they fell asleep while driving. You could fall asleep without any warning.

Tell your doctor right away if you fall asleep while you are doing activities such as talking, eating, driving, or if you feel sleepier than normal for you.

● low blood pressure when you sit or stand up quickly. After you have been sitting or lying down, stand up slowly until you know how pramipexole dihydrochloride extended-release tablets affect you. This may help reduce the following symptoms while you are taking pramipexole dihydrochloride extended-release tablets:

● dizziness

● nausea

● fainting

● sweating

● unusual urges. Some people who take certain medicines to treat Parkinson's disease, including pramipexole dihydrochloride extended-release tablets, have reported problems, such as gambling, compulsive eating, compulsive buying, and increased sex drive.

If you or your family members notice that you are developing unusual urges or behaviors, talk to your doctor.

● hallucinations and other psychotic-like behavior (seeing visions, hearing sounds or feeling sensations that are not real, confusion, excessive suspicion, aggressive behavior, agitation, delusional beliefs and disorganized thinking). The chances of having hallucinations or other psychotic-like changes are higher in people taking pramipexole dihydrochloride extended-release tablets for Parkinson's disease who are elderly (age 65 or older).

If you have hallucinations or other psychotic-like changes, talk with your doctor right away.

● uncontrolled sudden movements (dyskinesia). If you have new dyskinesia, or your existing dyskinesia gets worse, tell your doctor.

● posture changes. Talk with your doctor if you have posture changes you cannot control. These may include your neck bending forward, bending forward at the waist, or tilting sideways when you sit, stand, or walk.

●withdrawal symptoms. Pramipexole dihydrochloride extended-release tablet is a dopamine agonist medicine. Dopamine agonist medicines, including pramipexole dihydrochloride extended-release tablets, can cause withdrawal symptoms as your dose is slowly lowered (tapered) or when treatment with pramipexole dihydrochloride extended-release tablets is stopped. Tell your doctor right away if you get any of the following withdrawal symptoms:

● fever

● confusion

● severe muscle stiffness

● feeling like you do not care about things you usually care about (apathy)

● anxiety

● depression

● fatigue

● insomnia

● sweating

● pain

After you have stopped taking pramipexole dihydrochloride extended-release tablets, your doctor may need to restart you at a low dose of pramipexole dihydrochloride extended-release tablets if you get severe withdrawal symptoms.

The most common side effects in people taking pramipexole dihydrochloride extended-release tablets for early Parkinson's disease are:

- nausea and vomiting
- constipation
- dizziness
- fatigue
- dry mouth
- swelling of the feet and ankles

The most common side effects in people taking pramipexole dihydrochloride extended-release tablets who have later stage Parkinson's disease are nausea, constipation, headache and weight loss (anorexia).

These are not all the possible side effects of pramipexole dihydrochloride extended-release tablets. Tell your doctor if you have any side effect that bothers you.

Call your doctor for medical advice about side effects. You may report side effects to FDA at 1-800-FDA-1088.

How should I store pramipexole dihydrochloride extended-release tablets?

- Store pramipexole dihydrochloride extended-release tablets at room temperature from 68ºF to 77ºF (20ºC to 25ºC).
- Keep pramipexole dihydrochloride extended-release tablets away from high humidity or moisture.
- Keep pramipexole dihydrochloride extended-release tablets and all medicines out of the reach of children.

General Information about the safe and effective use of pramipexole dihydrochloride extended-release tablets.

Medicines are sometimes prescribed for purposes other than those listed in a Patient Information leaflet. Do not use pramipexole dihydrochloride extended-release tablets for a condition for which it was not prescribed. Do not give pramipexole dihydrochloride extended-release tablets to other people, even if they have the same symptoms that you have. It may harm them.

This Patient Information leaflet summarizes the most important information about pramipexole dihydrochloride extended-release tablets. If you would like more information, talk with your doctor. You can ask your pharmacist or doctor for more information about pramipexole dihydrochloride extended-release tablets that is written for healthcare professionals.

For current Prescribing Information, contact Ingenus Pharmaceuticals, LLC Toll-Free at 1-877-748-1970.

What are the ingredients in pramipexole dihydrochloride extended-release tablets?

Active Ingredient: pramipexole dihydrochloride monohydrate.

Inactive Ingredients: hypromellose, corn starch, microcrystalline cellulose, sodium lauryl sulfate, sodium metabisulfite and magnesium stearate.

What do pramipexole dihydrochloride extended-release tablets look like?

These pictures show what pramipexole dihydrochloride extended-release tablets look like. Notice that each strength tablet looks different. Immediately call your pharmacist if you receive a pramipexole dihydrochloride extended-release tablet that does not look like one of the tablets shown below, as you may have received the wrong medication.

Tablets not actual size.

This Patient Information has been approved by the U.S. Food and Drug Administration.

Rev.B

Iss: Jul 2024

Manufactured for:

Ingenus Pharmaceuticals, LLC

Orlando, FL 32811-7193

Made in China